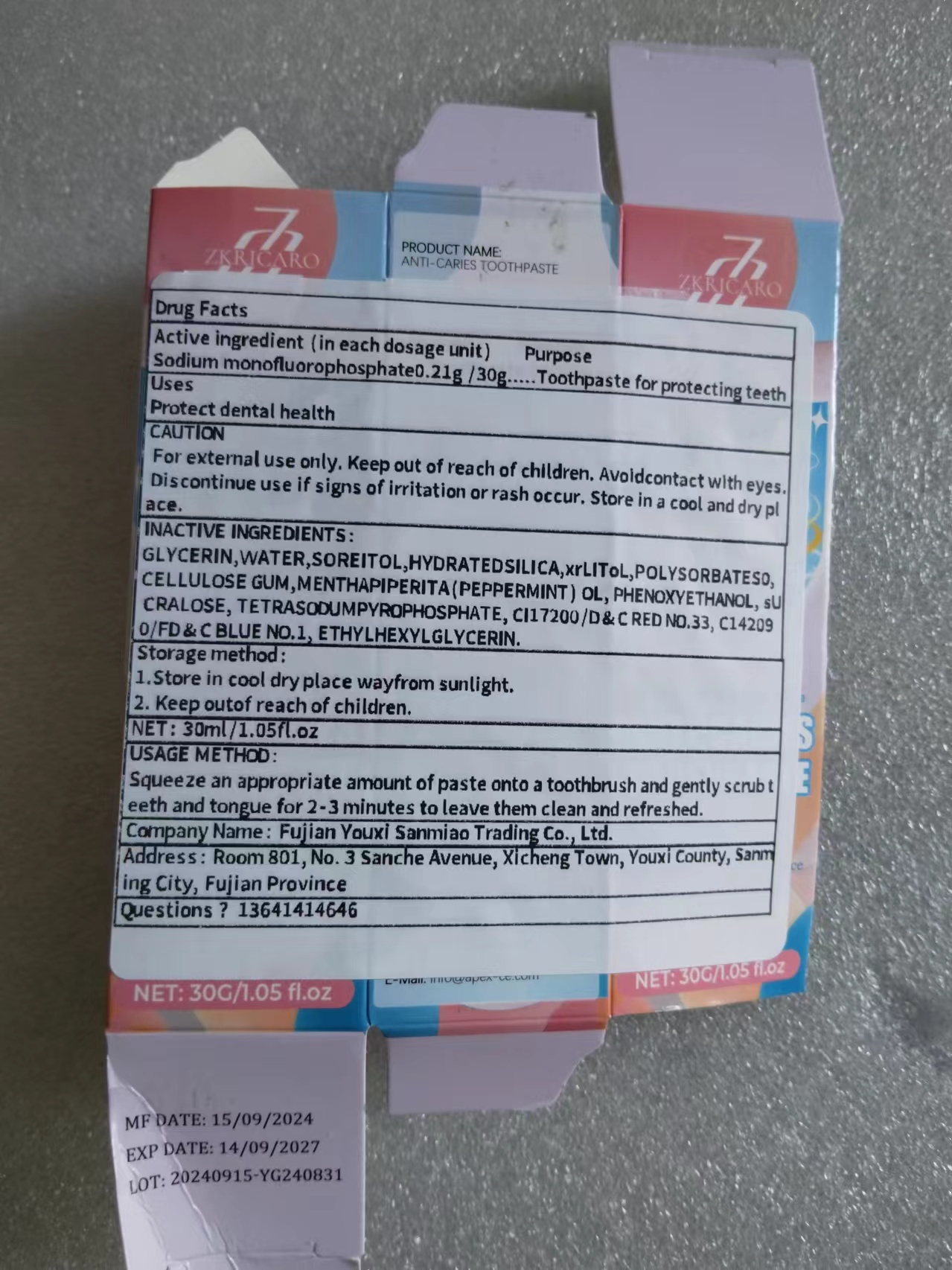 DRUG LABEL: Anti caries
NDC: 84518-005 | Form: PASTE
Manufacturer: Fujian Youxi Sanmiao Trading Co., Ltd.
Category: otc | Type: HUMAN OTC DRUG LABEL
Date: 20241107

ACTIVE INGREDIENTS: SODIUM FLUORIDE 0.21 g/30 g
INACTIVE INGREDIENTS: GLYCERIN; HYDRATED SILICA; WATER; TETRASODIUM PYROPHOSPHATE; D&C RED NO. 33; POLAWAX POLYSORBATE; ETHYLHEXYLGLYCERIN; PHENOXYETHANOL; CELLULOSE GUM; MENTHOL, UNSPECIFIED FORM; FD&C BLUE NO. 1; SUCRALOSE

Active ingredients: Sodium monofluorophosphate 0.21g/30g

Purpose: Toothpaste for protecting teeth

INDICATIONS AND USAGE

1. Prevent tooth decay: During the brushing process, fluoride can be attached to the surface of the teeth to form a protective layer to prevent bacterial erosion.

2. Clean dental plaque: Fluoride has a redox effect, which can make the dental plaque attached to the surface of the teeth fall off.

Warnings section

For external use only. Keep out of reach of children. Avoidcontact with eyes. Discontinue use if signs of irritation or rash occur.

Dosage & administration section

Squeeze an appropriate amount of paste onto a toothbrush and gently scrub teeth and tongue for 2-3 minutes to leave them clean and refreshed.

INACTIVE INGREDIENTS:

GLYCERIN, AQuA, HYDRATED SILICA, POLYSORBATE S0, CELLULOSE GUM,MENTHAPIPERITA(PEPPERMINT) OL, PHENOXYETHANOL, sUCRALOSE, TETRASODUMPYROPHOSPHATE, CI17200/D&C RED NO.33, C1 42090/FD&C BLUE NO.1, ETHYLHEXYLGLYCERIN.

KEEP OUT OF REACH OF CHILDREN

For external use only. Keep out of reach of children. Avoidcontact with eyes. Discontinue use if signs of irritation or rash occur.

Label